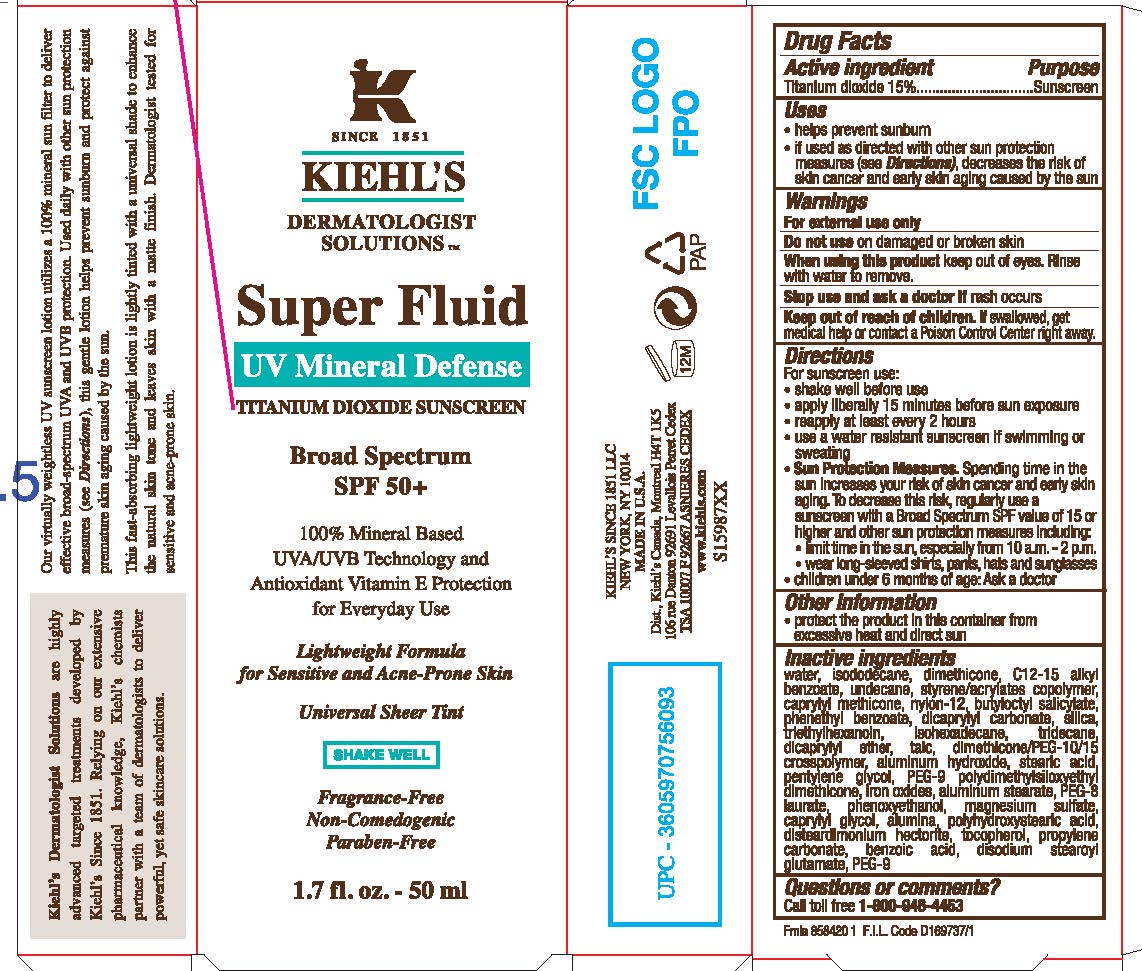 DRUG LABEL: Kiehls Since 1851 Dermatologist Solutions SuperFluid UV Mineral Defense Broad Spectrum SPF 50 Plus Sunscreen
NDC: 49967-409 | Form: LOTION
Manufacturer: L'Oreal USA Products Inc
Category: otc | Type: HUMAN OTC DRUG LABEL
Date: 20231230

ACTIVE INGREDIENTS: TITANIUM DIOXIDE 150 mg/1 mL
INACTIVE INGREDIENTS: WATER; ISODODECANE; DIMETHICONE; ALKYL (C12-15) BENZOATE; UNDECANE; CAPRYLYL TRISILOXANE; NYLON-12; BUTYLOCTYL SALICYLATE; PHENETHYL BENZOATE; DICAPRYLYL CARBONATE; SILICON DIOXIDE; TRIETHYLHEXANOIN; ISOHEXADECANE; TRIDECANE; DICAPRYLYL ETHER; TALC; ALUMINUM HYDROXIDE; STEARIC ACID; PENTYLENE GLYCOL; PEG-9 POLYDIMETHYLSILOXYETHYL DIMETHICONE; FERRIC OXIDE RED; ALUMINUM STEARATE; PEG-8 LAURATE; PHENOXYETHANOL; MAGNESIUM SULFATE, UNSPECIFIED FORM; CAPRYLYL GLYCOL; ALUMINUM OXIDE; DISTEARDIMONIUM HECTORITE; TOCOPHEROL; PROPYLENE CARBONATE; BENZOIC ACID; DISODIUM STEAROYL GLUTAMATE; POLYETHYLENE GLYCOL 450

Drug Facts

Active ingredient

Titanium dioxide 15%

Purpose

Sunscreen

Uses

- helps prevent sunburn
- if used as directed with other sun protection measures (see Directions), decreases the risk of skin cancer and early skin aging caused by the sun

Warnings

For external use only

Do not use

on damaged or broken skin

When using this product

keep out of eyes. Rinse with water to remove.

Stop use and ask a doctor if

rash occurs

Keep out of reach of children.

If swallowed, get medical help or contact a Poison Control Center right away.

Directions

For sunscreen use:

- shake well before use
- apply liberally 15 minutes before sun exposure
- reapply at least every 2 hours
- use a water resistant sunscreen if swimming or sweating
- Sun Protection Measures. Spending time in the sun increases your risk of skin cancer and early skin aging. To decrease this risk, regularly use a sunscreen with a Broad Spectrum SPF value of 15 or higher and other sun protection measures including:

● limit time in the sun, especially from 10 a.m. – 2 p.m.

● wear long-sleeved shirts, pants, hats, and sunglasses

- children under 6 months of age: Ask a doctor

Other information

protect the product in this container from excessive heat and direct sun

Inactive ingredients

water, isododecane, dimethicone, C12-15 alkyl benzoate, undecane, styrene/acrylates copolymer, caprylyl methicone, nylon-12, butyloctyl salicylate, phenethyl benzoate, dicaprylyl carbonate, silica, triethylhexanoin, isohexadecane, tridecane, dicaprylyl ether, talc, dimethicone/PEG-10/15 crosspolymer, aluminum hydroxide, stearic acid, pentylene glycol, PEG-9 polydimethylsiloxyethyl dimethicone, iron oxides, aluminum stearate, PEG-8 laurate, phenoxyethanol, magnesium sulfate, caprylyl glycol, alumina, polyhydroxystearic acid, disteardimonium hectorite, tocopherol, propylene carbonate, benzoic acid, disodium stearoyl glutamate, PEG-9

Questions or comments?

Call toll free 1-800-946-4453